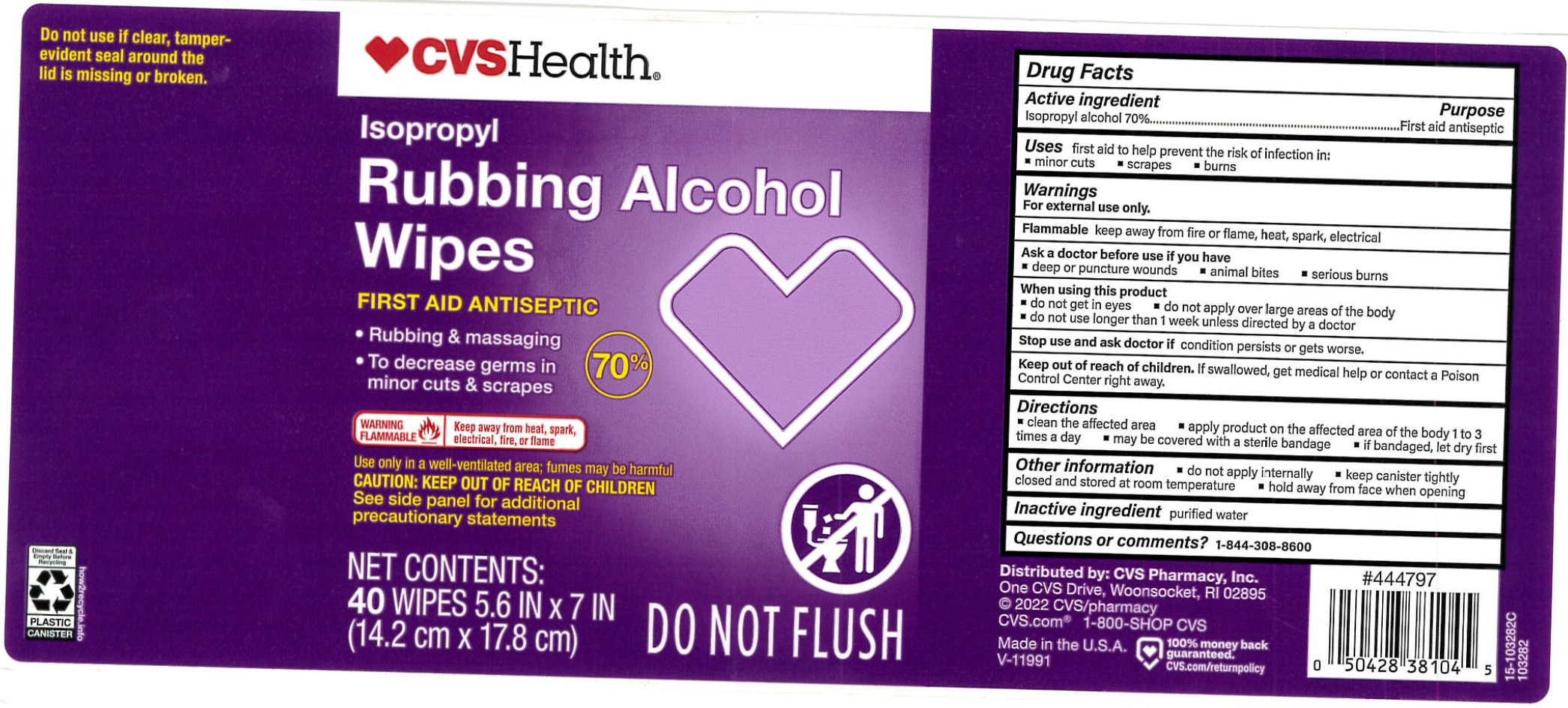 DRUG LABEL: CVS Health Isopropyl Rubbing Alcohol
NDC: 59779-756 | Form: CLOTH
Manufacturer: CVS Health
Category: otc | Type: HUMAN OTC DRUG LABEL
Date: 20231110

ACTIVE INGREDIENTS: ISOPROPYL ALCOHOL 0.7 g/1 g
INACTIVE INGREDIENTS: WATER

CVS Health Isopropyl Rubbing Alcohol

Active Ingredient

Isopropyl alcohol 70%

Purpose

First aid antiseptic

Use

first aid to help prevent to the risk of infection in:

- minor cuts
- scrapes
- burns

Warnings:

keep away from fire or flame, heat, spark, electrical For external use only Flammable

Ask a doctor before use if you have

- deep or pucture wounds
- animal bites
- serious burns

When using this product

- do not get in eyes
- do not apply over large areas of the body
- do not use longer than 1 week unless directed by a doctor

Stop use and ask a doctor if

condition persists or gets worse.

Keep out of reach of children.

If sawllowed, get medical help or contact a Poison Control Center right away.

Directions

- clean the affected area
- apply product on the affected area of the body 1 to 3 times a day
- may be covered with a sterile bandage
- if bandaged, let dry first

Other Information

- do not apply internally
- keep canister tightly closed and stored at room temperature
- hold away from face when opening

Inactive ingredient

purified water

Questions or comments?

1-844-308-8600